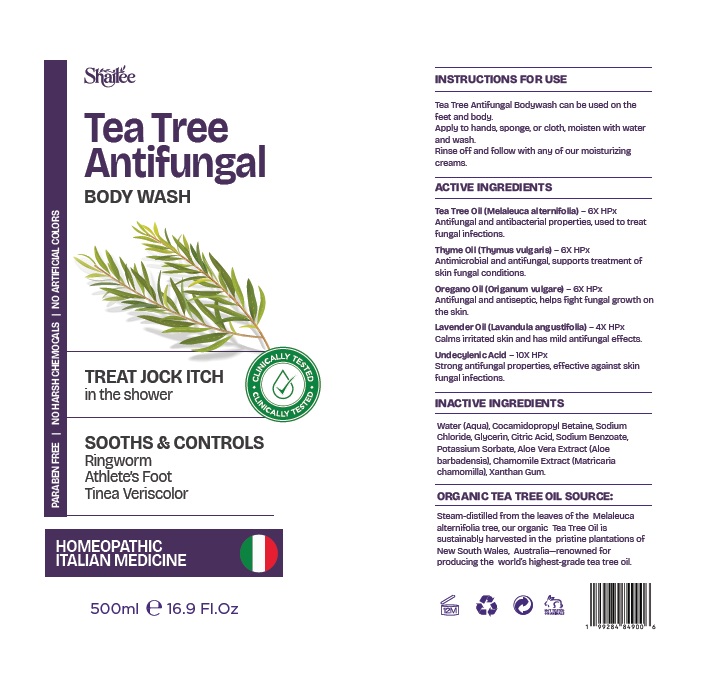 DRUG LABEL: Shailee Tea Tree Body Wash
NDC: 84938-009 | Form: LIQUID
Manufacturer: Foshan Sugar Max Cosmetics CO.,Ltd
Category: homeopathic | Type: HUMAN OTC DRUG LABEL
Date: 20251105

ACTIVE INGREDIENTS: TEA TREE OIL 6 [hp_X]/500 mL; LAVENDER OIL 4 [hp_X]/500 mL; OREGANO LEAF OIL 6 [hp_X]/500 mL; UNDECYLENIC ACID 10 [hp_Q]/500 mL; THYME OIL 6 [hp_X]/500 mL
INACTIVE INGREDIENTS: COCAMIDOPROPYL BETAINE; GLYCERIN; WATER; ANHYDROUS CITRIC ACID; SODIUM BENZOATE; POTASSIUM SORBATE; ALOE VERA LEAF; MATRICARIA CHAMOMILLA WHOLE; XANTHAN GUM; SODIUM CHLORIDE

Active ingredient Purpose

Tea Tree Oil (Melaleuca alternifolia) 6X HPx Antifungal treatment

Thyme Oil (Thymus vulgaris) – 6X HPx Antifungal treatment

Oregano Oil 6X HPx Antifungal treatment

Lavender Oil (Lavandula angustifolia) 4X HPx Antifungal treatment

Undecylenic Acid 10X HPx Antifungal treatment

Uses

For the treatment of most
● jock itch (tinea cruris)
● ringworm (tinea corporis)
● athlete's foot (tinea pedis)
● tinea versicolor
For relief of:
● itching
● scaling
● cracking
● burning
● irritation

Warnings

For external use only

Ask a doctor before useon children under 2 years of age.

When using this product, avoid contact with the eyes. If contact occurs rinse thoroughly with water.

Stop use and ask a doctor if
● irritation occurs
● there is no improvement within 2 weeks (4 weeks for ringworm, athlete's foot, and tinea versicolor).

Keep out of reach of children. If swallowed, get medical help or contact a Poison Control Center right away.

Direactions

Read all package directions and warnings before use.
● Use only as directed.
● Clean the affected area with Anti-Fungal Wash and warm water, rinse and dry
thoroughly.
● For best results, leave on for 1-2 minutes before rinsing and drying.
● Use twice daily (morning and night), or as directed by a doctor.
● This product is not effective on scalp or nails.
● For jock itch, use daily for 2 weeks.
● For ringworm, tinea versicolor and athlete's foot, use daily for 4 weeks. If condition
persists longer, consult a doctor.
● For athlete's foot: pay special attention to spaces between the toes; wear well-fitting,
ventilated shoes, and change shoes and socks at least once daily.
● Intended for use by normally healthy adults only.
● Persons under 18 years of age or those with highly sensitive or allergic skin should
use only as directed by a doctor.
● Supervise children in the use of this product.

Inactive ingredients

Water (Aqua), Cocamidopropyl Betaine, Sodium Chloride, Glycerin, Citric Acid, Sodium Benzoate, Potassium Sorbate, Aloe Vera Extract (Aloe
barbadensis), Chamomile Extract (Matricaria chamomilla), Xanthan Gum.